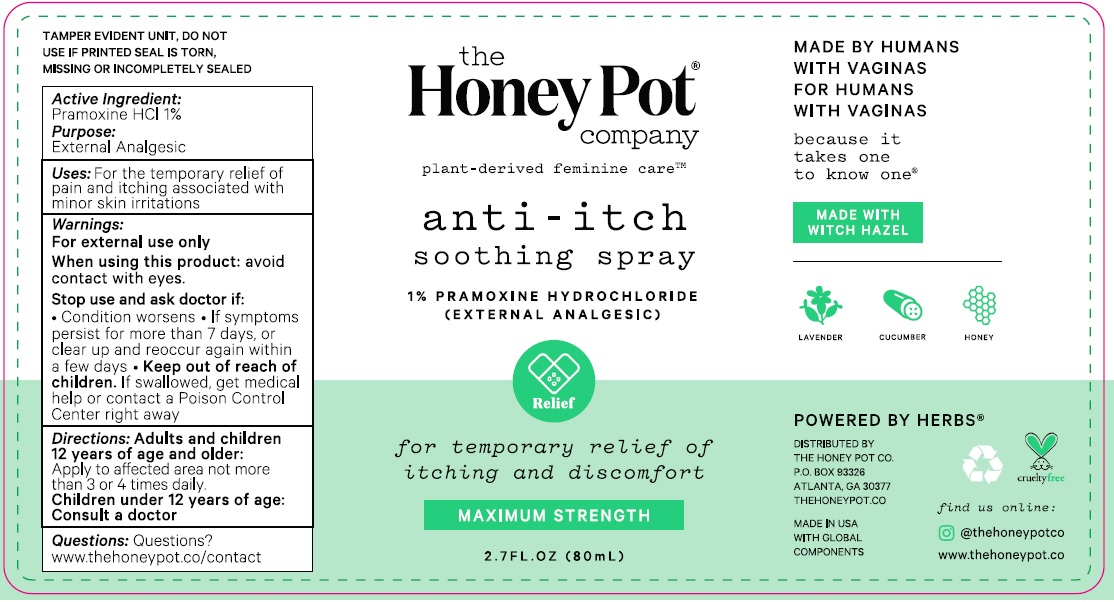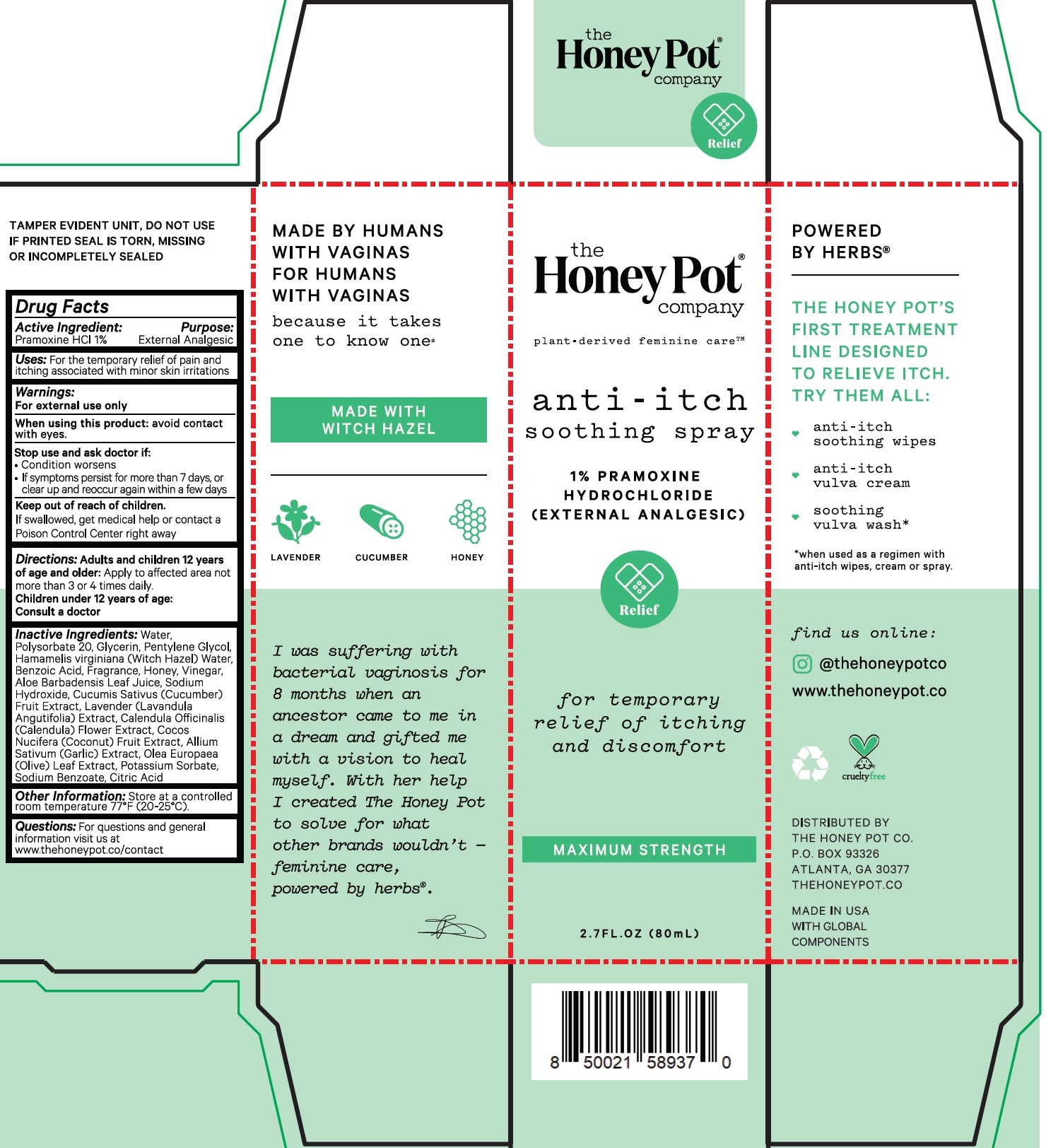 DRUG LABEL: Anti Itch Soothing 1 Pramoxine Hydrochloride
NDC: 82637-9370 | Form: SPRAY
Manufacturer: The Honey Pot Company LLC
Category: otc | Type: HUMAN OTC DRUG LABEL
Date: 20240801

ACTIVE INGREDIENTS: PRAMOXINE HYDROCHLORIDE 10 mg/1 mL
INACTIVE INGREDIENTS: WATER; POLYSORBATE 20; GLYCERIN; PENTYLENE GLYCOL; HAMAMELIS VIRGINIANA ROOT BARK/STEM BARK; BENZOIC ACID; HONEY; ACETIC ACID; ALOE VERA LEAF; SODIUM HYDROXIDE; CUCUMBER; LAVANDULA ANGUSTIFOLIA SUBSP. ANGUSTIFOLIA FLOWER; CALENDULA OFFICINALIS FLOWER; COCONUT; GARLIC; OLEA EUROPAEA LEAF; POTASSIUM SORBATE; SODIUM BENZOATE; CITRIC ACID MONOHYDRATE

The Honey Pot Anti-Itch Soothing Spray

Active Ingredient:

Pramoxine HCl 1%

Purpose:

External Analgesic

Uses:

For the temporary relief of pain and itching associated with minor skin irritations

Warnings:

For external use only

When using this product:

avoid contact with eyes.

Stop use and ask doctor if:

- Condition worsens
- If symptoms persist for more than 7 days, or clear up and reoccur again within a few days

Keep out of reach of children.

If swallowed, get medical help or contact a Poison Control Center right away

Directions:

Apply to affected not more than 3 or 4 times daily. Adults and children 12 years of age and older:

Children under 12 years of age: Consult a doctor

Inactive Ingredients:

Water, Polysorbate 20, Glycerin, Pentylene Glycol, Hamamelis virginiana (Witch Hazel) Water, Benzoic Acid, Fragrance, Honey, Vinegar, Aloe Barbadensis Leaf Juice, Sodium Hydroxide, Cucumis Sativus (Cucumber) Fruit Extract, Lavender (Lavandula Angutifolia) Extract, Calendula Officinalis (Calendula) Flower Extract, Cocos Nucifera (Coconut) Fruit Extract, Allium Sativum (Garlic) Extract, Olea Europaea (Olive) Leaf Extract, Potassium Sorbate, Sodium Benzoate, Citric Acid

Other Information:

Store at a controlled room temperature 77°F (20-25°C).

Questions:

For questions and general information visit us at www.thehoneypot.co/contact